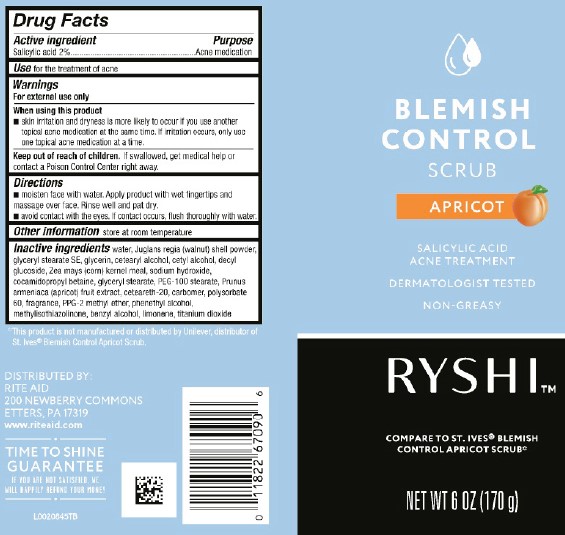 DRUG LABEL: Medicated Apricot Scrub
NDC: 11822-7001 | Form: GEL
Manufacturer: Rite Aid Corporation
Category: otc | Type: HUMAN OTC DRUG LABEL
Date: 20260130

ACTIVE INGREDIENTS: SALICYLIC ACID 19.8 mg/1 g
INACTIVE INGREDIENTS: WATER; JUGLANS REGIA SHELL; GLYCERYL STEARATE SE; GLYCERIN; CETOSTEARYL ALCOHOL; CETYL ALCOHOL; DECYL GLUCOSIDE; CORN GRAIN; SODIUM HYDROXIDE; COCAMIDOPROPYL BETAINE; GLYCERYL MONOSTEARATE; PEG-100 STEARATE; APRICOT JUICE; CETYL ACETATE; POLYOXYL 20 CETOSTEARYL ETHER; CARBOMER HOMOPOLYMER, UNSPECIFIED TYPE; POLYSORBATE 60; ACETYLATED LANOLIN ALCOHOLS; PPG-2 METHYL ETHER; .ALPHA.-ISOBUTYLPHENETHYL ALCOHOL; BENZYL ALCOHOL; LIMONENE, (+)-; METHYLISOTHIAZOLINONE; TITANIUM DIOXIDE

Ryshi_Daylogic 041.006/041AK
Medicated Apricot Scrub

Active ingredient

Salicylic acid 2%

Purpose

Acne medication

Use

for the treatment of acne

Warnings

For external use only

When using this product

- skin irritation and dryness is more likely to occure if you use another topical acne medication at the same time. If irritation occurs, only use one topical acne medication at a time.

Keep out of reach of children.

If swallowed, get medical help or contact a Poison Control Center right away.

Directions

- moisten face with water. Apply product with wet fingertips and massage over face. Rinse well and pat dry.
- avoid contact with the eyes. If contact occurs, flush thoroughly with water.

Other information

Store at room temperature

Inactive ingredients

water, Juglans regia (walnut) shell powder, glyceryl stearate SE, glycerin, cetearyl alcohol, cetyl alcohol, decyl glucoside, Zea mays (corn) kernel meal, sodium hydroxide, cocamidopropyl betaine, glyceryl stearate, PEG-100 stearate, Prunus armeniaca (apricot) fruit extract, ceteareth-20, carbomer, polysorbate 60, fragrance, PPG-2 methyl ether, phenethyl alcohol, methylisothiazolinone, benzyl alcohol, limonene, titanium dioxide

Disclaimer

*This product is not manufactured or distributed by Unilever, distributor of St. Ives®Blemish Control Apricot Scrub.

Adverse reaction

DISTRIBUTED BY:

RITE AID

3O HUNTER LANE

CAMP HILL, PA 17011

www.riteaid.com

TIME TO SHINE GUARANTEE

IF YOU'RE NOT SATISFIED, WE'LL HAPPILY REFUND YOUR MONEY

Principal display panel

Blemish Control Scrub

Apricot

Salicylic Acid Acne Treatment

Dermatologist Tested

NON-GREASY

RYSHI™

Compare to St. Ives® Blemish Control Apricot Scrub*

NET WT 6 OZ (170 g)